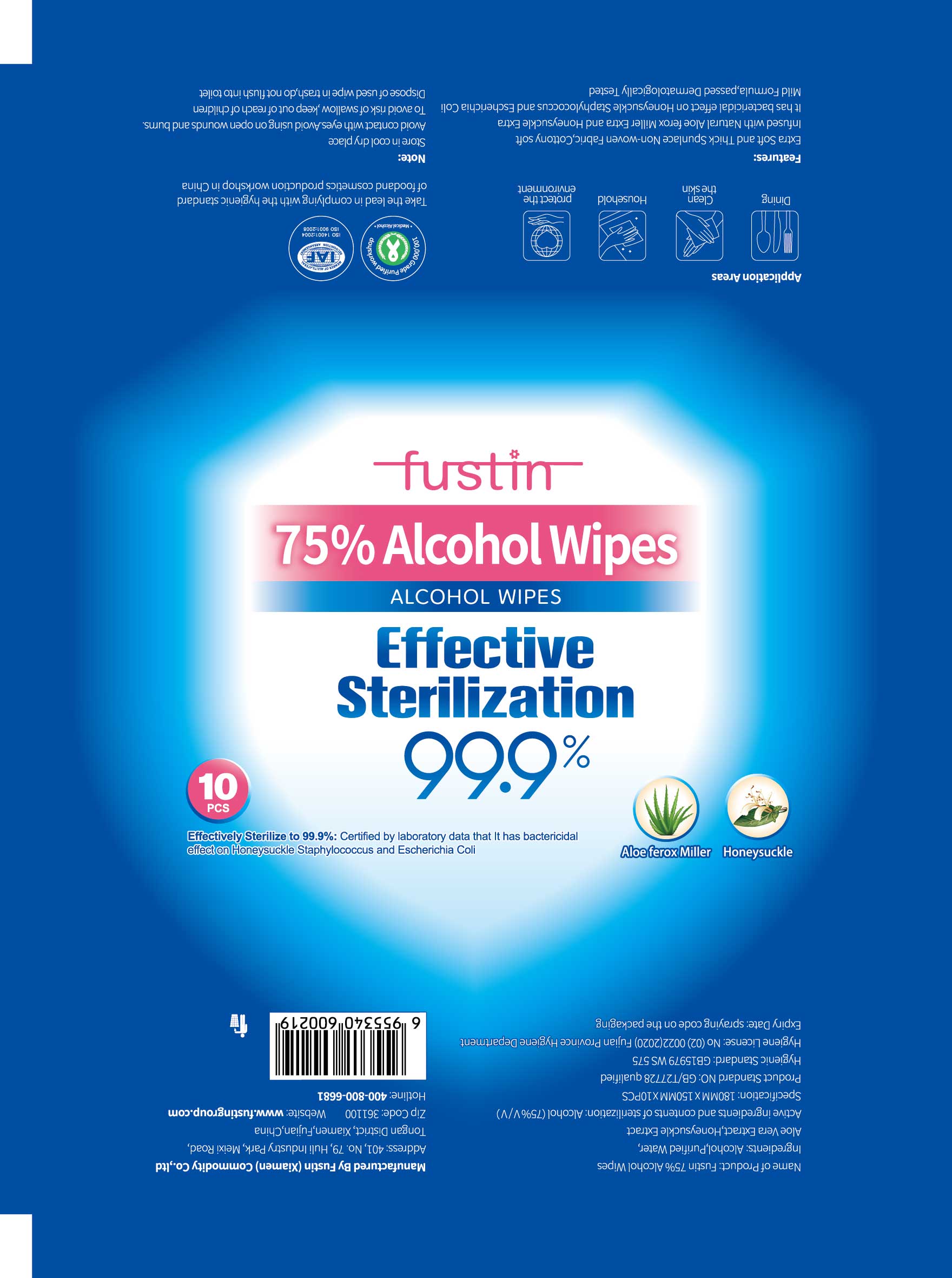 DRUG LABEL: Fustin Alcohol Wipes
NDC: 56136-308 | Form: SWAB
Manufacturer: Ganzhou Olivee Cosmetic Co., Ltd.
Category: otc | Type: HUMAN OTC DRUG LABEL
Date: 20200417

ACTIVE INGREDIENTS: ALCOHOL 75 g/100 g
INACTIVE INGREDIENTS: water; ALOE VERA LEAF

Alcohol Wipes

Active Ingredient

Alcohol 75% V/V

Purpose

Antibeatrial

USE

●For hand sanitizing to decrease bacteria on the skin.
●Apply topically to the skin to help prevent cross contamination.

Warning

- Flammable, keep away from fire or flame. For external use only.
- Avoid contact with eyes
- Avoid using on open wounds and burns
- To avoid risk of swallow, keep out of children
- Dispose of used wipe in trash, do not flush into toilet

●Keep out of reach of children unless under adult supervision. If swallowed, get medical help or contact a Poison Contrl Center immediately.

Directions

●Open lid, gently pull back resealable label, remove and use wipe as required.
●Reseal back after use to avoid evaporation of alcohol.

Inactive ingredients

Purified Water, Aloe Vera Extract, Honeysuckle Extract